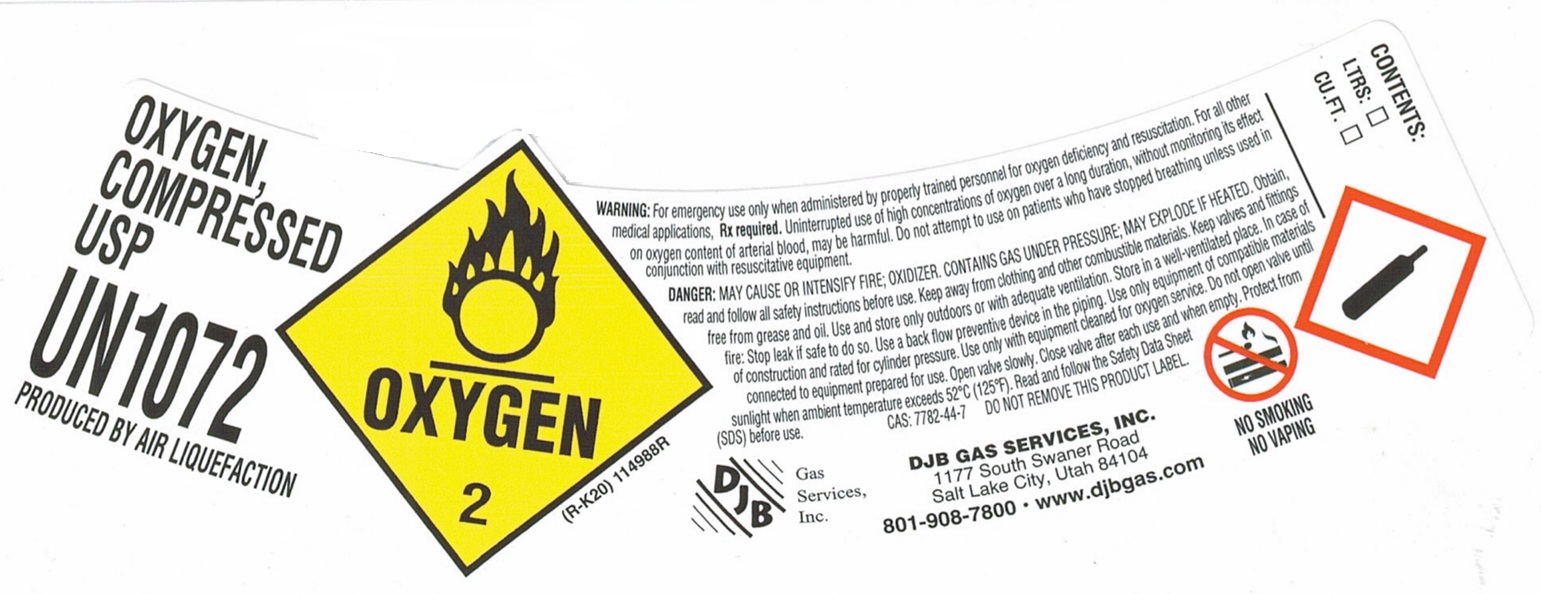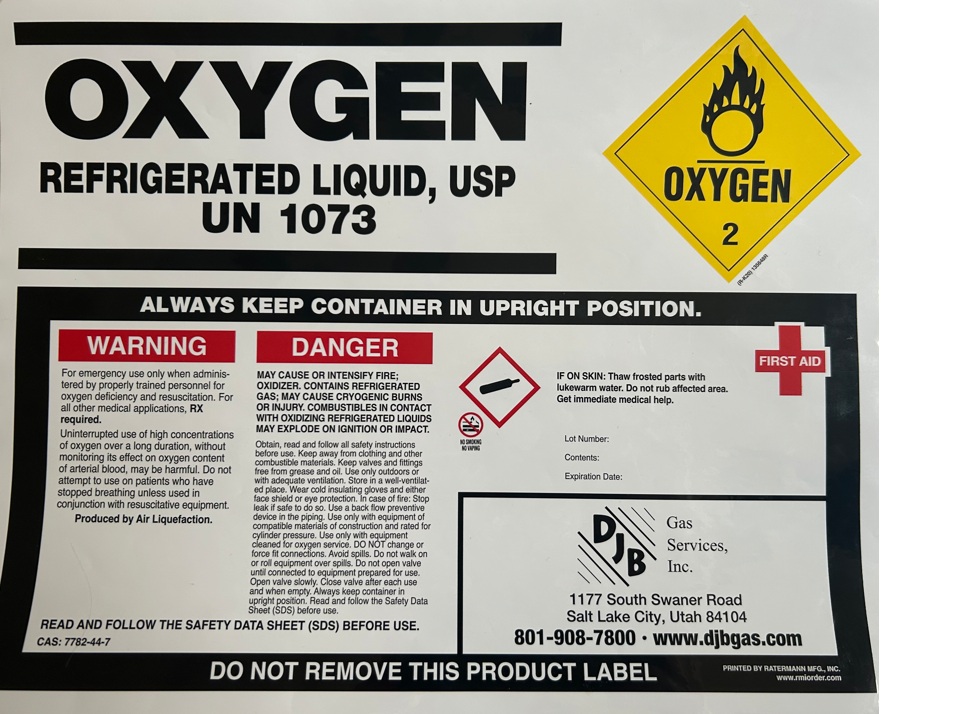 DRUG LABEL: Oxygen
NDC: 43621-001 | Form: GAS
Manufacturer: DJB Gas Services, Inc
Category: prescription | Type: HUMAN PRESCRIPTION DRUG LABEL
Date: 20260226

ACTIVE INGREDIENTS: OXYGEN 990 mL/1 L

Oxygen

PACKAGE LABEL

OXYGEN, COMPRESSED USP

UN1072

PRODUCED BY AIR LIQUEFACTION

WARNING: For emergency use only when administered by properly trained personnel for oxygen deficiency and resuscitation. For all other medical applications, Rx required. Uninterrupted use of high concentrations of oxygen over a long duration, without monitoring its effect on oxygen content of arterial blood, may be harmful. Do not attempt to use on patients who have stopped breathing unless used in conjunction with resuscitative equipment.

DANGER: MAY CAUSE OR INTENSIFY FIRE; OXIDIZER. CONTAINS GAS UNDER PRESSURE; MAY EXPLODE IF HEATED. Obtain, read and follow all safety instructions before use. Keep away from clothing and other combustible materials. Keep valves and fittings free from grease and oil. Use and store only outdoors or with adequate ventilation. Store in a well-ventilated place. In case of fire: Stop leak if safe to do so. Use a back flow preventive device in the piping. Use only equipment of compatible materials of construction and rated for cylinder pressure. Use only with equipment cleaned for oxygen service. Do not open valve until connected to equipment prepared for use. Open valve slowly. Close valve after each use and when empty. Protect form sunlight when ambient temperature exceeds 52 C (125 F). Read and follow the Safety Data Sheet (SDS) before use. CAS: 7782-44-7 DO NOT REMOVE THIS PRODUCT LABEL.

DJB Gas Services, Inc.

DJB GAS SERVICES, INC.

1177 Swaner Road

Salt Lake City, UT 84104

801-908-7800 www.djbgas.com

NO SMOKING

NO VAPING

CONTENTS: LTRS: CU.FT.

PACKAGE LABEL

OXYGEN

REFRIGERATED LIQUID, USP

UN 1073

ALWAYS KEEP CONTAINER IN UPRIGHT POSITION.

WARNING

For emergency use only when administered by properly trained personnel for oxygen deficiency and resuscitation. For all other medical applications, Rx required.

Uninterrupted use of high concentrations of oxygen over a long duration, without monitoring its effect on oxygen content of arterial blood, may be harmful. Do not attempt to use on patients who have stopped breathing unless used in conjunction with resuscitative equipment.

Produced by Air Liquefaction.

DANGER

MAY CAUSE OR INTENSIFY FIRE; OXIDIZER. CONTAINS REFRIGERATED GAS; MAY CAUSE CRYOGENIC BURNS OR INJURY. COMBUSTIBLES IN CONTACT WITH OXIDIZING REFRIGERATED LIQUIDS MAY EXPLODE ON IGNITION OR IMPACT.

Obtain, read and follow all safety instructions before use. Keep away from clothing and other combustible materials. Keep valves and fittings free from grease and oil. Use only outdoors or with adequate ventilation. Store in a well-ventilated place. Wear cold insulating gloves and either face shield or eye protection. In case of fire: Stop leak if safe to do so. Use a back flow preventive device in the piping. Use only with equipment of compatible materials of construction and rated for cylinder pressure. Use only with equipment cleaned for oxygen service. DO NOT change or force fit connections. Avoid spills. Do not walk on or roll equipment over spills. Do not open valve until connected to equipment prepared for use. Open valve slowly. Close valve after each use and when empty. Always keep container in upright position. Read and follow the Safety Data Sheet (SDS) before use.

READ AND FOLLOW THE SAFETY DATA SHEET (SDS) BEFORE USE.

CAS: 7782-44-7

NO SMOKING

NO VAPING

FIRST AID

IF ON SKIN: Thaw frosted parts with lukewarm water. Do not rub affected area. Get immediate medical help.

Lot Number:

Contents:

Expiration Date:

DJB Gas Services, Inc.

1177 Swaner Road

Salt Lake City, UT 84104

801-908-7800 www.djbgas.com

DO NOT REMOVE THIS PRODUCT LABEL